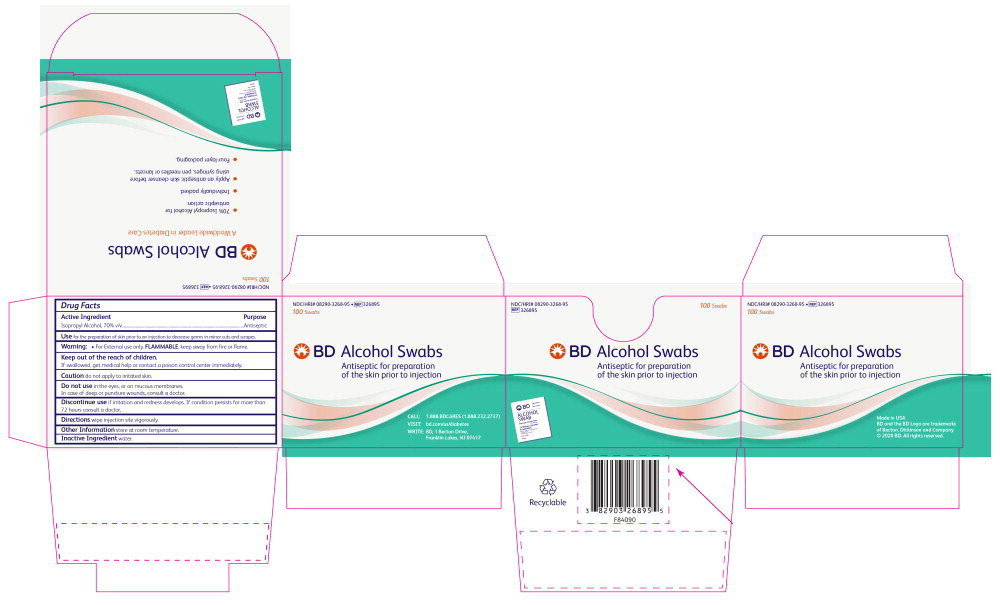 DRUG LABEL: Isopropyl Alcohol
NDC: 8290-3268 | Form: SWAB
Manufacturer: Becton Dickinson and Company
Category: otc | Type: HUMAN OTC DRUG LABEL
Date: 20241003

ACTIVE INGREDIENTS: Isopropyl Alcohol 0.75 g/1 1
INACTIVE INGREDIENTS: Water

Drug Facts

Active Ingredient

Isopropyl Alcohol, 70% v/v

Purpose

Antiseptic

Use

for the preparation of skin prior to an injection to decrease germs in minor cuts and scrapes.

Warning:

- For External use only. FLAMMABLE, keep away from fire or flame.

Keep out of the reach of children.

If swallowed, get medical help or contact a poison control center immediately.

Caution do not apply to irritated skin.

Do not use in the eyes, or on mucous membranes.

In case of deep or puncture wounds, consult a doctor.

STOP USE

Discontinue use if irritation and redness develops. If condition persists for more than 72 hours, consult a doctor.

Directions

wipe injection site vigorously.

Other Information

store at room temperature.

Inactive Ingredient

water.

Principal Display Panel – Carton Label.

NDC/HRI# 08290-3268-95

326895

100 Swabs

BD Alcohol Swabs

Antiseptic for preparation of the skin prior to injection

CALL: 1.888.BDCARES (1.888.232.2737)

VISIT: www.bd.com/us/diabetes

WRITE: BD, 1 Becton Drive, Franklin Lakes, NJ 07417